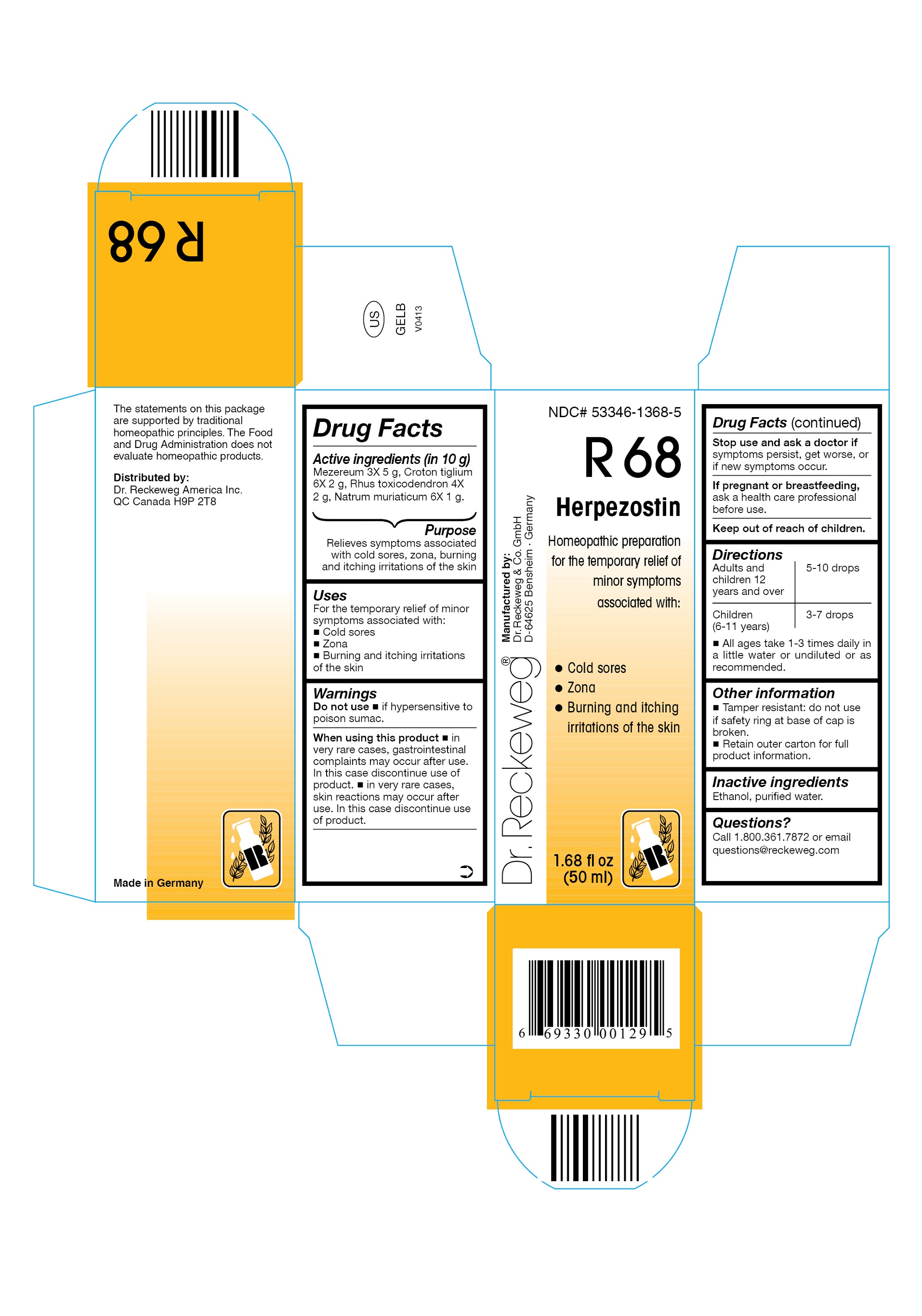 DRUG LABEL: DR. RECKEWEG R68 Herpezostin
NDC: 53346-1368 | Form: LIQUID
Manufacturer: PHARMAZEUTISCHE FABRIK DR. RECKEWEG & CO
Category: homeopathic | Type: HUMAN OTC DRUG LABEL
Date: 20130403

ACTIVE INGREDIENTS: DAPHNE MEZEREUM BARK 3 [hp_X]/50 mL; CROTON TIGLIUM SEED 6 [hp_X]/50 mL; TOXICODENDRON PUBESCENS LEAF 4 [hp_X]/50 mL; SODIUM CHLORIDE 6 [hp_X]/50 mL
INACTIVE INGREDIENTS: ALCOHOL; WATER

DR. RECKEWEG R68 Herpezostin

Active ingredients

Mezereum 3X 5 g, Croton tiglium 6X 2 g, Rhus toxicodendron 4X 2 g, Natrum muriaticum 6X 1 g in 10 g.

Purpose

Relieves symptoms associated with cold sores, zona, burning and itching irritations of the skin

Uses

For the temporary relief of minor symptoms associated with:

- Cold sores
- Zona
- Burning and itching irritations of the skin

Warnings

Do not use

- if hypersensitive to poison sumac.

When using this product

- in very rare cases, gastrointestinal complaints may occur after use. In this case discontinue use of product.
- in very rare cases, skin reactions may occur after use. In this case discontinue use of product.

Stop use and ask a doctor if symptoms persist, get worse, or if new symptoms occur.

PREGNANCY OR BREAST FEEDING

If pregnant or breastfeeding, ask a health care professional before use.

Keep out of reach of children.

Directions

Adults and children ≥ 12 years 5-10 drops, children (6-11 years) 3-7 drops, all ages take 1-3 times daily in a little water or undiluted or as recommended.

Other information

- Tamper resistant: do not use if safety ring at base of cap is broken.
- Retain outer carton for full product information.

Inactive ingredients

Ethanol, purified water.

Questions?

Call 1-800-361-7872 or email questions@reckeweg.com

PACKAGE LABEL

NDC# 53346-1368-5

Dr. Reckeweg R68 Herpezostin

Homeopathic preparation for the temporary relief of minor symptoms associated with:

- Cold sores
- Zona
- Burning and itching irritations of the skin

Manufactured by:

Dr. Reckeweg Co. GmbH

D-64625 Bensheim

Germany

1.68 fl oz
(50 ml)